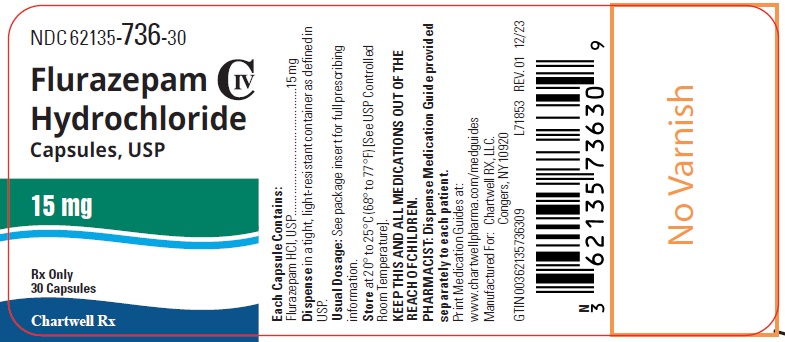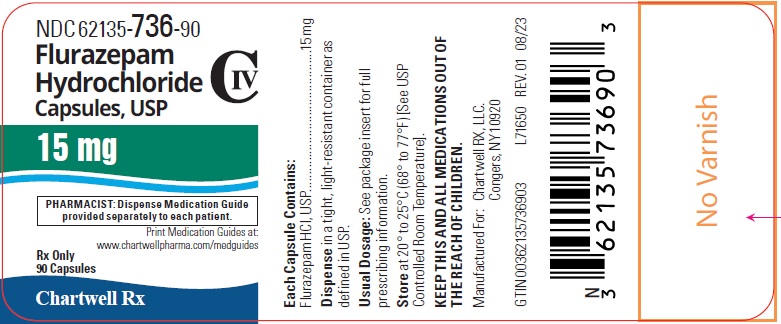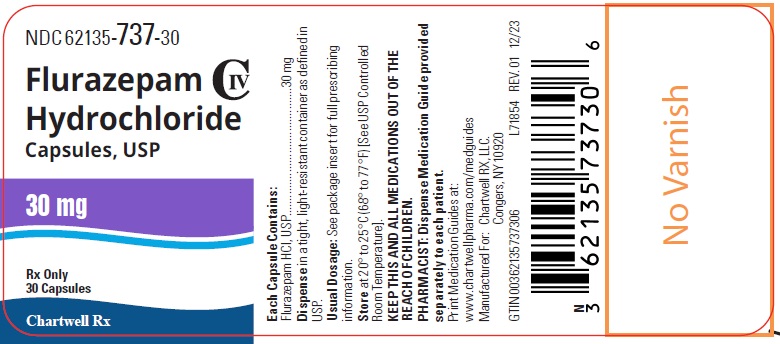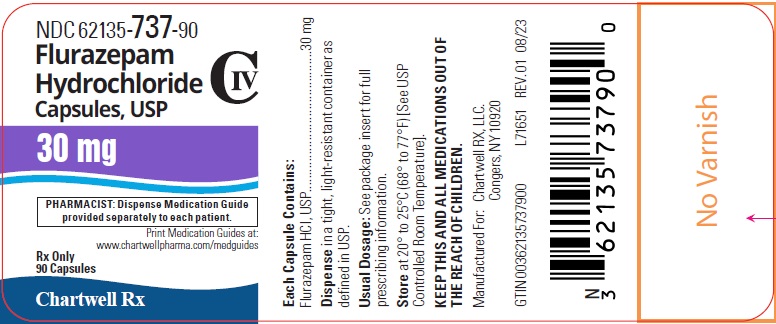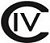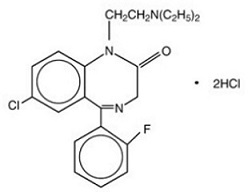 DRUG LABEL: Flurazepam Hydrochloride
NDC: 62135-736 | Form: CAPSULE
Manufacturer: Chartwell RX, LLC
Category: prescription | Type: HUMAN PRESCRIPTION DRUG LABEL
Date: 20241028
DEA Schedule: CIV

ACTIVE INGREDIENTS: FLURAZEPAM HYDROCHLORIDE 15 mg/1 1
INACTIVE INGREDIENTS: ANHYDROUS LACTOSE; SILICON DIOXIDE; FD&C BLUE NO. 1; FD&C RED NO. 3; GELATIN, UNSPECIFIED; MANNITOL; MAGNESIUM STEARATE; TALC; TITANIUM DIOXIDE; FERROSOFERRIC OXIDE; BUTYL ALCOHOL; ALCOHOL; ISOPROPYL ALCOHOL; POTASSIUM HYDROXIDE; PROPYLENE GLYCOL; SHELLAC; AMMONIA; WATER

HIGHLIGHTS OF PRESCRIBING INFORMATION

Flurazepam Hydrochloride Capsules, USP
These highlights do not include all the information needed to use FLURAZEPAM HYDROCHLORIDE CAPSULES safely and effectively. See full prescribing information for FLURAZEPAM HYDROCHLORIDE CAPSULES.
FLURAZEPAM HYDROCHLORIDE capsules, for oral use CIV
Initial U.S. Approval: 1970

WARNING: RISKS FROM CONCOMITANT USE WITH OPIOIDS; ABUSE, MISUSE, AND ADDICTION; and DEPENDENCE AND WITHDRAWAL REACTIONS

See full prescribing information for complete boxed warning.

- Concomitant use of benzodiazepines and opioids may result in profound sedation, respiratory depression, coma, and death. Reserve concomitant prescribing of these drugs in patients for whom alternative treatment options are inadequate. Limit dosages and durations to the minimum required. Follow patients for signs and symptoms of respiratory depression and sedation (5.1, 7.1).

- The use of benzodiazepines, including flurazepam hydrochloride capsules, exposes users to risks of abuse, misuse, and addiction, which can lead to overdose or death. Before prescribing flurazepam hydrochloride capsules and throughout treatment, assess each patient’s risk for abuse, misuse, and addiction (5.2).

- Abrupt discontinuation or rapid dosage reduction of flurazepam hydrochloride capsules after continued use may precipitate acute withdrawal reactions, which can be life-threatening. To reduce the risk of withdrawal reactions, use a gradual taper to discontinue flurazepam hydrochloride capsules or reduce the dosage (2.3, 5.3).

1 INDICATIONS AND USAGE

Flurazepam, a gamma-aminobutyric (GABAA) agonist, is indicated for the treatment of insomnia characterized by difficulty falling asleep, frequent nocturnal awakenings, and/or early morning awakenings. (1)

2 DOSAGE AND ADMINISTRATION

- Use the lowest dose effective for the patient.
- Recommended initial dose is 15 mg for women and 15 mg or 30 mg for men. (2.1)
- Elderly or debilitated patients: recommended dose is 15 mg. (2.2)

3 DOSAGE FORMS AND STRENGTHS

- 15 mg and 30 mg capsules. (3)

4 CONTRAINDICATIONS

- Hypersensitivity to flurazepam or other benzodiazepines. (4)

5 WARNINGS AND PRECAUTIONS

- CNS depressant effects: Impaired alertness and motor coordination, including risk of falling. Daytime impairment. Caution patients against driving and other activities requiring complete mental alertness. (5.4)
- The failure of insomnia to remit after 7 to 10 days of treatment may indicate the presence of a primary psychiatric and/or medical illness that should be evaluated. (5.5)
- Severe anaphylactic/anaphylactoid reactions: Angioedema and anaphylaxis have been reported. Do not rechallenge if such reactions occur. (5.6)
- Sleep driving and other complex behaviors while not fully awake: Risk increases with dose and concomitant CNS depressants and alcohol. Immediately evaluate any new onset behavioral changes. (5.7)
- Worsening of depression or suicidal thinking may occur: Prescribe the least number of capsules feasible to avoid intentional overdose. (5.8)
- Neonatal Sedation and Withdrawal Syndrome: Flurazepam use during pregnancy can result in neonatal sedation and/or neonatal withdrawal. (5.9)

6 ADVERSE REACTIONS

Adverse reactions: dizziness, drowsiness, light-headedness, staggering, ataxia, falling. (6.1)

To report SUSPECTED ADVERSE REACTIONS, contact Chartwell RX, LLC. at 1-845-232-1683 or FDA at 1-800-FDA-1088 or www.fda.gov/medwatch.

7 DRUG INTERACTIONS

- Concomitant use of benzodiazepines and opioids may result in profound sedation, respiratory depression, and death. (7.1)
- CNS Depressants: Downward dose adjustment may be necessary due to additive effects. (7.2)

8 USE IN SPECIFIC POPULATIONS

- Lactation: Breastfeeding not recommended. (8.2)

FULL PRESCRIBING INFORMATION

WARNING: RISKS FROM CONCOMITANT USE WITH OPIOIDS; ABUSE, MISUSE, AND ADDICTION; and DEPENDENCE AND WITHDRAWAL REACTIONS

- Concomitant use of benzodiazepines and opioids may result in profound sedation, respiratory depression, coma, and death. Reserve concomitant prescribing of these drugs in patients for whom alternative treatment options are inadequate. Limit dosages and durations to the minimum required. Follow patients for signs and symptoms of respiratory depression and sedation [see Warnings and Precautions (5.1) and Drug Interactions (7.1) ].
- The use of benzodiazepines, including flurazepam hydrochloride capsules, exposes users to risks of abuse, misuse, and addiction, which can lead to overdose or death. Abuse and misuse of benzodiazepines commonly involve concomitant use of other medications, alcohol, and/or illicit substances, which is associated with an increased frequency of serious adverse outcomes. Before prescribing flurazepam hydrochloride capsules, and throughout treatment, assess each patient’s risk for abuse, misuse, and addiction [ see Warnings and Precautions (5.2) ].
- The continued use of benzodiazepines, including flurazepam hydrochloride capsules, may lead to clinically significant physical dependence. The risks of dependence and withdrawal increase with longer treatment duration and higher daily dose. Abrupt discontinuation or rapid dosage reduction of flurazepam hydrochloride capsules after continued use may precipitate acute withdrawal reactions, which can be life-threatening. To reduce the risk of withdrawal reactions, use a gradual taper to discontinue flurazepam hydrochloride capsules or reduce the dosage [ see Dosage and Administration (2.3) and Warnings and Precautions (5.3) ].

1 INDICATIONS AND USAGE

Flurazepam hydrochloride capsules are indicated for the treatment of insomnia characterized by difficulty in falling asleep, frequent nocturnal awakenings, and/or early morning awakenings [see Clinical Studies (14) ].

Since insomnia is often transient and intermittent, short-term use is usually sufficient. Prolonged use of hypnotics is usually not indicated and should only be undertaken concomitantly with appropriate evaluation of the patient.

2 DOSAGE AND ADMINISTRATION

2.1 Dosage in Adults

Use the lowest dose effective for the patient, as important adverse effects of flurazepam hydrochloride capsules are dose related.

The recommended initial dose is 15 mg for women and either 15 mg or 30 mg for men. The 15 mg dose can be increased to 30 mg if necessary for efficacy.

The recommended initial doses for women and men are different because flurazepam clearance is lower in women [see Pharmacokinetics (12.3) ].

2.2 Dosage in Elderly or Debilitated Patients

Elderly or debilitated patients may be especially sensitive to flurazepam. Since the risk of the development of oversedation, dizziness, confusion and/or ataxia increases substantially with larger doses in elderly or debilitated patients, it is recommended that in such patients the dosage be limited to 15 mg. Staggering and falling have also been reported, particularly in geriatric patients [see Warnings and Precautions (5.2) ].

2.3 Discontinuation or Dosage Reduction of Flurazepam Hydrochloride Capsules

To reduce the risk of withdrawal reactions, use a gradual taper to discontinue flurazepam hydrochloride capsules or reduce the dosage. If a patient develops withdrawal reactions, consider pausing the taper or increasing the dosage to the previous tapered dosage level. Subsequently decrease the dosage more slowly [ see Warnings and Precautions (5.3) and Drug Abuse and Dependence (9.3) ].

3 DOSAGE FORMS AND STRENGTHS

Flurazepam Hydrochloride Capsules, USP are available containing either 15 mg or 30 mg of Flurazepam Hydrochloride, USP.

Flurazepam Hydrochloride Capsules, USP 15 mg are Size #2 hard gelatin capsules, Blue opaque cap with white opaque body, imprinted with “ CE” on the cap and “ 28” on the body with black ink, filled with white to off-white powder.

Flurazepam Hydrochloride Capsules, USP 30 mg are Size #2 hard gelatin capsules, Blue opaque cap with white opaque body, imprinted with “ CE” on the cap and “ 29” on the body with black ink, filled with white to off-white powder.

4 CONTRAINDICATIONS

Flurazepam hydrochloride capsules are contraindicated in patients with known hypersensitivity to flurazepam or other benzodiazepines. Rare cases of angioedema involving the tongue, glottis or larynx have been reported in patients after taking the first or subsequent doses of flurazepam. Some patients have had additional symptoms such as dyspnea, throat closing, or nausea and vomiting that suggest anaphylaxis. Patients who develop such reactions should not be rechallenged with flurazepam.

5 WARNINGS AND PRECAUTIONS

5.1 Risks from Concomitant Use of Opioids

Concomitant use of benzodiazepines, including flurazepam, and opioids may result in profound sedation, respiratory depression, coma, and death. Because of these risks, reserve concomitant prescribing of benzodiazepines and opioids in patients for whom alternative treatment options are inadequate.

Observational studies have demonstrated that concomitant use of opioid analgesics and benzodiazepines increases the risk of drug-related mortality compared to use of opioids alone. If a decision is made to prescribe flurazepam concomitantly with opioids, prescribe the lowest effective dosages and minimum durations of concomitant use, and follow patients closely for signs and symptoms of respiratory depression and sedation. Advise both patients and caregivers about the risks of respiratory depression and sedation when flurazepam is used with opioids [see Drug Interactions (7)].

5.2 Abuse, Misuse, and Addiction

The use of benzodiazepines, including flurazepam hydrochloride capsules, exposes users to the risks of abuse, misuse, and addiction, which can lead to overdose or death. Abuse and misuse of benzodiazepines often (but not always) involve the use of doses greater than the maximum recommended dosage and commonly involve concomitant use of other medications, alcohol, and/or illicit substances, which is associated with an increased frequency of serious adverse outcomes, including respiratory depression, overdose, or death [see Drug Abuse and Dependence (9.2) ].

Before prescribing flurazepam hydrochloride capsules and throughout treatment, assess each patient’s risk for abuse, misuse, and addiction (e.g., using a standardized screening tool). Use of flurazepam hydrochloride capsules, particularly in patients at elevated risk, necessitates counseling about the risks and proper use of flurazepam hydrochloride capsules along with monitoring for signs and symptoms of abuse, misuse, and addiction. Prescribe the lowest effective dosage; avoid or minimize concomitant use of CNS depressants and other substances associated with abuse, misuse, and addiction (e.g., opioid analgesics, stimulants); and advise patients on the proper disposal of unused drug. If a substance use disorder is suspected, evaluate the patient and institute (or refer them for) early treatment, as appropriate.

5.3 Dependence and Withdrawal Reactions

To reduce the risk of withdrawal reactions, use a gradual taper to discontinue flurazepam hydrochloride capsules or reduce the dosage (a patient-specific plan should be used to taper the dose) [see Dosage and Administration (2.3)] . Patients at an increased risk of withdrawal adverse reactions after benzodiazepine discontinuation or rapid dosage reduction include those who take higher dosages, and those who have had longer durations of use.

Acute Withdrawal Reactions:The continued use of benzodiazepines, including flurazepam hydrochloride capsules, may lead to clinically significant physical dependence. Abrupt discontinuation or rapid dosage reduction of flurazepam hydrochloride capsules after continued use, or administration of flumazenil (a benzodiazepine antagonist) may precipitate acute withdrawal reactions, which can be life-threatening (e.g., seizures) [ see Drug Abuse and Dependence (9.3) ].

Protracted Withdrawal Syndrome:In some cases, benzodiazepine users have developed a protracted withdrawal syndrome with withdrawal symptoms lasting weeks to more than 12 months [ see Drug Abuse and Dependence (9.3) ].

5.4 CNS-Depressant Effects and Next-Day Impairment

Dizziness, drowsiness, light-headedness, staggering, ataxia and falling can occur, particularly in elderly or debilitated persons. Severe sedation, lethargy, disorientation and coma, probably indicative of drug intolerance or overdosage, have been reported.

Flurazepam is a central nervous system (CNS) depressant and can impair daytime function even when used as prescribed. Prescribers should monitor for excess depressant effects, but impairment can occur in the absence of subjective symptoms, and may not be reliably detected by ordinary clinical exam (i.e., less than formal psychomotor testing). While pharmacodynamic tolerance or adaptation to some adverse depressant effects of flurazepam may develop, patients using flurazepam should be cautioned against driving or engaging in other hazardous activities or activities requiring complete mental alertness.

Additive effects occur with concomitant use of other CNS depressants (e.g., other benzodiazepines, opioids, tricyclic antidepressants, alcohol). Downward dose adjustment of flurazepam and concomitant CNS depressants should be considered. The potential for adverse drug interactions continues for several days following discontinuation of flurazepam, until serum levels of psychoactive metabolites decline.

Use of flurazepam with other sedative-hypnotics is not recommended. Alcohol generally should not be used during treatment with flurazepam. The risk of next-day psychomotor impairment is increased if flurazepam is taken with less than a full night of sleep remaining (7 to 8 hours); if higher than the recommended dose is taken; if coadministered with other CNS depressants [see Dosage and Administration (2)].

Because flurazepam can cause drowsiness and a decreased level of consciousness, patients, particularly the elderly, are at higher risk of falls.

5.5 Need to Evaluate for Co-morbid Disorders

Because sleep disturbances may be the presenting manifestation of a physical and/or psychiatric disorder, symptomatic treatment of insomnia should be initiated only after a careful evaluation of the patient. The failure of insomnia to remit after 7 to 10 days of treatment may indicate the presence of a primary psychiatric and/or medical illness that should be evaluated. Worsening of insomnia or the emergence of new thinking or behavior abnormalities may be the consequence of an unrecognized psychiatric or physical disorder. Such findings have emerged during the course of treatment with sedative-hypnotic drugs.

5.6 Severe Anaphylactic or Anaphylactoid Reactions

Rare cases of angioedema involving the tongue, glottis or larynx have been reported in patients after taking the first or subsequent doses of sedative-hypnotics, including flurazepam. Some patients have had additional symptoms such as dyspnea, throat closing, or nausea and vomiting that suggest anaphylaxis.

Some patients have required medical therapy in the emergency department. If angioedema involves the tongue, glottis or larynx, airway obstruction may occur and be fatal. Patients who develop angioedema after treatment with flurazepam should not be rechallenged with the drug.

5.7 Abnormal Thinking and Behavior Changes

Abnormal thinking and behavior changes have been reported in patients treated with sedative-hypnotics including flurazepam. Some of these changes include decreased inhibition (e.g., aggressiveness and extroversion that seemed out of character), bizarre behavior, and depersonalization. Visual and auditory hallucinations have also been reported. Amnesia, and other neuro-psychiatric symptoms, may occur.

Paradoxical reactions such as stimulation, agitation, increased muscle spasticity, and sleep disturbances may occur unpredictably.

Complex behaviors such as “sleep-driving” (i.e., driving while not fully awake, with amnesia for the event) have been reported with use of sedative-hypnotics. These behaviors can occur with initial treatment or in patients previously tolerant of flurazepam or other sedative-hypnotics. Although these behaviors can occur with use at therapeutic doses, risk is increased by higher doses or concomitant use of alcohol or other CNS depressants. Due to risk to the patient and community, flurazepam should be discontinued if “sleep-driving” occurs.

Other complex behaviors (e.g., preparing and eating food, making phone calls, or having sex) have been reported in patients who are not fully awake after taking a sedative-hypnotic. As with sleep-driving, patients usually do not remember these events.

5.8 Worsening of Depression

Benzodiazepines may worsen depression. Consequently, appropriate precautions (e.g., limiting the total prescription size and increased monitoring for suicidal ideation) should be considered.

5.9 Neonatal Sedation and Withdrawal Syndrome

Use of flurazepam late in pregnancy can result in sedation (respiratory depression, lethargy, hypotonia) and/or withdrawal symptoms (hyperreflexia, irritability, restlessness, tremors, inconsolable crying, and feeding difficulties) in the neonate [see Use in Specific Populations (8.1)]. Monitor neonates exposed to flurazepam during pregnancy or labor for signs of sedation and monitor neonates exposed to flurazepam during pregnancy for signs of withdrawal; manage these neonates accordingly.

6 ADVERSE REACTIONS

The following serious adverse reactions are discussed in greater detail in other sections of the label:

- Risks from Concomitant Use with Opioids [see Warnings and Precautions (5.1) ]
- Abuse, Misuse, and Addiction [see Warnings and Precautions (5.2)]
- Dependence and Withdrawal Reactions [see Warnings and Precautions (5.3) ]
- CNS-depressant effects and next-day impairment [see Warnings and Precautions (5.4)]
- Severe Anaphylactic and Anaphylactoid Reactions [see Warnings and Precautions (5.6)]
- Abnormal thinking and behavior changes, and complex behaviors [see Warnings and Precautions (5.7)]
- Worsening of depression [see Warnings and Precautions (5.8)]
- Neonatal Sedation and Withdrawal Syndrome [see Warnings and Precautions (5.9)]

6.1 Clinical Trials Experience

Reported were headache, heartburn, upset stomach, nausea, vomiting, diarrhea, constipation, gastrointestinal pain, nervousness, talkativeness, apprehension, irritability, weakness, palpitations, chest pains, body and joint pains, and genitourinary complaints. There have also been rare occurrences of leukopenia, granulocytopenia, sweating, flushes, difficulty in focusing, blurred vision, burning eyes, faintness, hypotension, shortness of breath, pruritus, skin rash, dry mouth, bitter taste, excessive salivation, anorexia, euphoria, depression, slurred speech, confusion, restlessness, hallucinations and elevated SGOT, SGPT, total and direct bilirubin elevations, and elevated alkaline phosphatase.

7 DRUG INTERACTIONS

7.1 Opioids

The concomitant use of benzodiazepines and opioids increases the risk of respiratory depression because of actions at different receptor sites in the CNS that control respiration. Benzodiazepines interact at GABAAsites, and opioids interact primarily at mu receptors. When benzodiazepines and opioids are combined, the potential for benzodiazepines to significantly worsen opioid-related respiratory depression exists. Limit dosage and duration of concomitant use of benzodiazepines and opioids, and follow patients closely for respiratory depression and sedation.

7.2 CNS Depressants

Benzodiazepines, including flurazepam, produce additive CNS depressant effects when co-administered with ethanol or other CNS depressants (e.g., psychotropic medications, anticonvulsants, antihistamines). Downward dose adjustment of flurazepam and/or concomitant CNS depressants may be necessary because of additive effects.

8 USE IN SPECIFIC POPULATIONS

8.1 Pregnancy

Pregnancy Exposure Registry:

There is a pregnancy exposure registry that monitors pregnancy outcomes in women exposed to psychiatric medications, including flurazepam, during pregnancy. Healthcare providers are encouraged to register patients by calling the National Pregnancy Registry for Psychiatric Medications at 1-866-961-2388 or visiting online at https://womensmentalhealth.org/pregnancyregistry/.

Risk Summary

Neonates born to mothers using benzodiazepines late in pregnancy have been reported to experience symptoms of sedation and/or neonatal withdrawal [ see Warnings and Precautions (5.9) and Clinical Considerations]. Available data from published observational studies of pregnant women exposed to benzodiazepines do not report a clear association with benzodiazepines and major birth defects (see Data).

The background risk of major birth defects and miscarriage for the indicated population is unknown. All pregnancies have a background risk of birth defect, loss, or other adverse outcomes. In the U.S. general population, the estimated background risk of major birth defects and miscarriage in clinically recognized pregnancies is 2 to 4% and 15 to 20%, respectively.

Clinical Considerations

Fetal/Neonatal Adverse Reactions

Benzodiazepines cross the placenta and may produce respiratory depression, hypotonia, and sedation in neonates. Monitor neonates exposed to flurazepam during pregnancy or labor for signs of sedation, respiratory depression, hypotonia, and feeding problems. Monitor neonates exposed to HALCION during pregnancy for signs of withdrawal. Manage these neonates accordingly [see Warnings and Precautions (5.9)].

Data

Human Data

Published data from observational studies on the use of benzodiazepines during pregnancy do not report a clear association with benzodiazepines and major birth defects. Although early studies reported an increased risk of congenital malformations with diazepam and chlordiazepoxide, there was no consistent pattern noted. In addition, the majority of more recent case-control and cohort studies of benzodiazepine use during pregnancy, which were adjusted for confounding exposures to alcohol, tobacco and other medications, have not confirmed these findings.

Animal Data

Administration of flurazepam to pregnant animals did not indicate a risk for adverse effects on morphological development at clinically relevant doses; however, animal data for other benzodiazepines suggest that possibility of adverse developmental effects (including long-term effects on neurobehavioral and immunological function) following prenatal exposure.

8.2 Lactation

Risk Summary

There are no data on the presence of flurazepam in human or animal milk. There are reports of sedation, poor feeding and poor weight gain in infants exposed to benzodiazepines through breast milk. The effects of flurazepam on milk production are unknown. Because of the flurazepam’s long half-life, the potential for flurazepam to accumulate in breast milk, and the potential for serious adverse reactions, including sedation and withdrawal symptoms in breastfed infants, advise patients that breastfeeding is not recommended during treatment with flurazepam.

8.4 Pediatric Use

Safety and effectiveness in pediatric patients have not been established.

8.5 Geriatric Use

Flurazepam may cause confusion and over-sedation in the elderly. Elderly patients generally should be started on a low dose of flurazepam and observed closely.

Elderly or debilitated patients may be more sensitive to benzodiazepines, reflecting the greater frequency of decreased hepatic, renal, or cardiac function, and of concomitant disease or other drug therapy.

9 DRUG ABUSE AND DEPENDENCE

9.1 Controlled Substance

Flurazepam is a Schedule IV controlled substance.

9.2 Abuse

Flurazepam hydrochloride capsules are a benzodiazepine and a CNS depressant with a potential for abuse and addiction. Abuse is the intentional, non-therapeutic use of a drug, even once, for its desirable psychological or physiological effects. Misuse is the intentional use, for therapeutic purposes, of a drug by an individual in a way other than prescribed by a health care provider or for whom it was not prescribed. Drug addiction is a cluster of behavioral, cognitive, and physiological phenomena that may include a strong desire to take the drug, difficulties in controlling drug use (e.g., continuing drug use despite harmful consequences, giving a higher priority to drug use than other activities and obligations), and possible tolerance or physical dependence. Even taking benzodiazepines as prescribed may put patients at risk for abuse and misuse of their medication. Abuse and misuse may lead to addiction.

Abuse and misuse of benzodiazepines often (but not always) involve the use of doses greater than the maximum recommended dosage and commonly involve concomitant use of other medications, alcohol, and/or illicit substances, which is associated with an increased frequency of serious adverse outcomes, including respiratory depression, overdose, or death. Benzodiazepines are often sought by individuals who abuse drugs and other substances, and by individuals with addictive disorders [see Warnings and Precautions (5.2)] .

The following adverse reactions have occurred with benzodiazepine abuse and/or misuse: abdominal pain, amnesia, anorexia, anxiety, aggression, ataxia, blurred vision, confusion, depression, disinhibition, disorientation, dizziness, euphoria, impaired concentration and memory, indigestion, irritability, muscle pain, slurred speech, tremors, and vertigo.

The following severe adverse reactions have occurred with benzodiazepine abuse and/or misuse: delirium, paranoia, suicidal ideation and behavior, seizures, coma, breathing difficulty, and death. Death is more often associated with polysubstance use (especially benzodiazepines with other CNS depressants such as opioids and alcohol) .

9.3 Dependence

Physical Dependence: Flurazepam hydrochloride capsules may produce physical dependence from continued therapy. Physical dependence is a state that develops as a result of physiological adaptation in response to repeated drug use, manifested by withdrawal signs and symptoms after abrupt discontinuation or a significant dose reduction of a drug. Abrupt discontinuation or rapid dosage reduction of benzodiazepines or administration of flumazenil, a benzodiazepine antagonist, may precipitate acute withdrawal reactions, including seizures, which can be life- threatening. Patients at an increased risk of withdrawal adverse reactions after benzodiazepine discontinuation or rapid dosage reduction include those who take higher dosages (i.e., higher and/or more frequent doses) and those who have had longer durations of use [see Warnings and Precautions (5.3)].

To reduce the risk of withdrawal reactions, use a gradual taper to discontinue flurazepam hydrochloride capsules or reduce the dosage [see Dosage and Administration (2.3) and Warnings and Precautions (5.3)].

Acute Withdrawal Signs and Symptoms:Acute withdrawal signs and symptoms associated with benzodiazepines have included abnormal involuntary movements, anxiety, blurred vision, depersonalization, depression, derealization, dizziness, fatigue, gastrointestinal adverse reactions (e.g., nausea, vomiting, diarrhea, weight loss, decreased appetite), headache, hyperacusis, hypertension, irritability, insomnia, memory impairment, muscle pain and stiffness, panic attacks, photophobia, restlessness, tachycardia, and tremor. More severe acute withdrawal signs and symptoms, including life-threatening reactions, have included catatonia, convulsions, delirium tremens, depression, hallucinations, mania, psychosis, seizures, and suicidality.

Protracted Withdrawal Syndrome:Protracted withdrawal syndrome associated with benzodiazepines is characterized by anxiety, cognitive impairment, depression, insomnia, formication, motor symptoms (e.g., weakness, tremor, muscle twitches), paresthesia, and tinnitus that persists beyond 4 to 6 weeks after initial benzodiazepine withdrawal. Protracted withdrawal symptoms may last weeks to more than 12 months .As a result, there may be difficulty in differentiating withdrawal symptoms from potential re-emergence or continuation of symptoms for which the benzodiazepine was being used.

Tolerance:Tolerance to flurazepam hydrochloride capsules may develop from continued therapy. Tolerance is a physiological state characterized by a reduced response to a drug after repeated administration (i.e., a higher dose of a drug is required to produce the same effect that was once obtained at a lower dose). Tolerance to the therapeutic effect of flurazepam hydrochloride capsules may develop; however, little tolerance develops to the amnestic reactions and other cognitive impairments caused by benzodiazepines.

10 OVERDOSAGE

Overdosage of benzodiazepines is characterized by central nervous system depression ranging from drowsiness to coma. In mild to moderate cases, symptoms can include drowsiness, confusion, dysarthria, lethargy, hypnotic state, diminished reflexes, ataxia, and hypotonia. Rarely, paradoxical or disinhibitory reactions (including agitation, irritability, impulsivity, violent behavior, confusion, restlessness, excitement, and talkativeness) may occur. In severe overdosage cases, patients may develop respiratory depression and coma. Overdosage of benzodiazepines in combination with other CNS depressants (including alcohol and opioids) may be fatal [see Warnings and Precautions (5.2)] . Markedly abnormal (lowered or elevated) blood pressure, heart rate, or respiratory rate raise the concern that additional drugs and/or alcohol are involved in the overdosage.

In managing benzodiazepine overdosage, employ general supportive measures, including intravenous fluids and airway management. Flumazenil, a specific benzodiazepine receptor antagonist indicated for the complete or partial reversal of the sedative effects of benzodiazepines in the management of benzodiazepine overdosage, can lead to withdrawal and adverse reactions, including seizures, particularly in the context of mixed overdosage with drugs that increase seizure risk (e.g., tricyclic and tetracyclic antidepressants) and in patients with long-term benzodiazepine use and physical dependency. The risk of withdrawal seizures with flumazenil use may be increased in patients with epilepsy. Flumazenil is contraindicated in patients who have received a benzodiazepine for control of a potentially life-threatening condition (e.g., status epilepticus). If the decision is made to use flumazenil, it should be used as an adjunct to, not as a substitute for, supportive management of benzodiazepine overdosage. See the flumazenil injection Prescribing Information.

Consider contacting a poison center (1-800-222-1222), poisoncontrol.org, or a medical toxicologist for additional overdosage management recommendations.

11 DESCRIPTION

Flurazepam Hydrochloride, USP is chemically 7-chloro-1-[2-(diethylamino)ethyl]-5-(ο-fluro-phenyl)-1,3-dihydro-2 H-1,4- benzodiazepin-2-one dihydrochloride. It is a pale yellow, crystalline compound, freely soluble in alcohol and very soluble in water. It has a molecular weight of 460.81 and the following structural formula:

Each capsule, for oral administration, contains either 15 mg or 30 mg of Flurazepam Hydrochloride, USP. In addition, each capsule contains the following inactive ingredients: anhydrous lactose, colloidal silicon dioxide, FD&C Blue #1, FD&C Red #3, gelatin, mannitol, magnesium stearate, talc, and titanium dioxide.

Additionally, capsule shells of 15 mg and 30 mg are imprinted with black pharmaceutical ink. The compositions of the black pharmaceutical ink are black iron oxide, butyl alcohol, dehydrated alcohol, isopropyl alcohol, potassium hydroxide, propylene glycol, purified water, shellac, and strong ammonia solution.

12 CLINICAL PHARMACOLOGY

12.1 Mechanism of Action

Flurazepam, like other central nervous system agents of the 1,4-benzodiazepine class, presumably exerts its effects by binding to stereo-specific receptors at several sites within the central nervous system (CNS). The exact mechanism of action is unknown.

12.3 Pharmacokinetics

Flurazepam hydrochloride is rapidly absorbed from the gastro-intestinal tract. Flurazepam is rapidly metabolized and is excreted primarily in the urine. Following a single oral dose, peak flurazepam plasma concentrations ranging from 0.5 to 4.0 ng/mL occur at 30 to 60 minutes post-dosing. The harmonic mean apparent half-life of flurazepam is 2.3 hours. The blood level profile of flurazepam and its major metabolites was determined in man following the oral administration of 30 mg daily for 2 weeks. The N1-hydroxyethyl-flurazepam was measurable only during the early hours after a 30 mg dose and was not detectable after 24 hours. The major metabolite in blood was N1-desalkyl-flurazepam, which reached steady-state (plateau) levels after 7 to 10 days of dosing, at levels approximately 5- to 6-fold greater than the 24-hour levels observed on Day 1. The half-life of elimination of N1-desalkyl-flurazepam ranged from 47 to 100 hours. The major urinary metabolite is conjugated N1-hydroxyethyl-flurazepam which accounts for 22% to 55% of the dose. Less than 1% of the dose is excreted in the urine as N1-desalkyl-flurazepam.

This pharmacokinetic profile may be responsible for the clinical observation that flurazepam is increasingly effective on the second or third night of consecutive use and that for 1 or 2 nights after the drug is discontinued both sleep latency and total wake time may still be decreased.

The single dose pharmacokinetics of flurazepam were studied in 12 healthy geriatric subjects (aged 61 to 85 years). The mean elimination half-life of desalkyl-flurazepam was longer in elderly male subjects (160 hours) compared with younger male subjects (74 hours), while mean elimination half-life was similar in geriatric female subjects (120 hours) and younger female subjects (90 hours). After multiple dosing, mean steady-state plasma levels of desalkyl-flurazepam were higher in elderly male subjects (81 ng/mL) compared with younger male subjects (53 ng/mL), while values were similar between elderly female subjects (85 ng/mL) and younger female subjects (86 ng/mL). The mean washout half-life of desalkyl-flurazepam was longer in elderly male and female subjects (126 and 158 hours, respectively) compared with younger male and female subjects (111 and 113 hours, respectively).^1

^1Greenblatt DJ, Divoll M, Hammatz JS, MacLauglin DS, Shader RI: Kinetics and clinical effects of flurazepam in young and elderly noninsomniacs. Clin Pharmacol Ther 30: 475-486, 1981.

13 NONCLINICAL TOXICOLOGY

Carcinogenesis, Mutagenesis, Impairment of Fertility

Studies to assess the genotoxic or carcinogenic potential of flurazepam or the effects of flurazepam on fertility have not been conducted.

14 CLINICAL STUDIES

Sleep laboratory studies have objectively determined that flurazepam hydrochloride capsules are effective for at least 28 consecutive nights of drug administration.

16 HOW SUPPLIED/STORAGE AND HANDLING

Flurazepam Hydrochloride Capsules, USP are available containing either 15 mg or 30 mg of Flurazepam Hydrochloride, USP.

Flurazepam Hydrochloride Capsules, USP 15 mg are Size #2 hard gelatin capsules, Blue opaque cap with white opaque body, imprinted with “ CE” on the cap and “ 28” on the body with black ink, filled with white to off-white powder.

They are available as follows,

Bottle of 30's - NDC 62135-736-30
Bottle of 90’s - NDC 62135-736-90

Flurazepam Hydrochloride Capsules, USP 30 mg are Size #2 hard gelatin capsules, Blue opaque cap with white opaque body, imprinted with “ CE” on the cap and “ 29” on the body with black ink, filled with white to off-white powder.

They are available as follows,

Bottle of 30's - NDC 62135-737-30
Bottle of 90’s - NDC 62135-737-90

Store at 20° to 25°C (68° to 77°F) [See USP Controlled Room Temperature].

Protect from light and moisture.

Dispense in a tight, light-resistant container as defined in the USP using a child-resistant closure.

PHARMACIST:Dispense a Medication Guide with each prescription.

17 PATIENT COUNSELING INFORMATION

Advise the patient to read the FDA-approved patient labeling (Medication Guide).

Risks from Concomitant Use with Opioids:Advise both patients and caregivers about the risks of potentially fatal respiratory depression and sedation when flurazepam hydrochloride capsules are used with opioids and not to use such drugs concomitantly unless supervised by a healthcare provider [see Warnings and Precautions (5.1), Drug Interactions (7.1)].

Abuse, Misuse, and Addiction:Inform patients that the use of flurazepam hydrochloride capsules, even at recommended dosages, exposes users to risks of abuse, misuse, and addiction, which can lead to overdose and death, especially when used in combination with other medications (e.g., opioid analgesics), alcohol, and/or illicit substances .Inform patients about the signs and symptoms of benzodiazepine abuse, misuse, and addiction; to seek medical help if they develop these signs and/or symptoms; and on the proper disposal of unused drug [see Warnings and Precautions (5.2) and Drug Abuse and Dependence (9.2)].

Withdrawal Reactions:Inform patients that the continued use of flurazepam hydrochloride capsules may lead to clinically significant physical dependence and that abrupt discontinuation or rapid dosage reduction of flurazepam hydrochloride capsules may precipitate acute withdrawal reactions, which can be life-threatening. Inform patients that in some cases, patients taking benzodiazepines have developed a protracted withdrawal syndrome with withdrawal symptoms lasting weeks to more than 12 months. Instruct patients that discontinuation or dosage reduction of flurazepam hydrochloride capsules may require a slow taper [see Warnings and Precautions (5.3) and Drug Abuse and Dependence (9.3)].

CNS Depressant Effects and Next-Day Impairment:Tell patients that flurazepam can cause next-day impairment, even in the absence of symptoms. Caution patients against driving or engaging in other hazardous activities or activities requiring complete mental alertness when using flurazepam. Tell patients that daytime impairment may persist for several days following discontinuation of flurazepam. Advise patients that increased drowsiness and decreased consciousness may increase the risk of falls in some patients [see Warnings and Precautions (5.4)].

Abnormal Thinking and Behavior Change:Instruct patients that sedative hypnotics can cause abnormal thinking and behavior change, including “sleep-driving” and other complex behaviors while not being fully awake (preparing and eating food, making phone calls, or having sex). Tell patients to call you immediately if they develop any of these symptoms [see Warnings and Precautions (5.7)].

Severe Allergic Reactions:Inform patients that severe allergic reactions can occur from flurazepam. Describe the signs/symptoms of these reactions and advise patients to seek medical attention immediately if these occur.

Worsening of Depression:Tell patients that flurazepam can worsen depression, and to immediately report any suicidal thoughts [see Warnings and Precautions (5.8)].

Alcohol and Other Drugs:Ask patients about alcohol consumption, medicines they are taking now, and drugs they may be taking without a prescription. Advise patients that alcohol generally should not be used during treatment with flurazepam.

Pregnancy:Advise pregnant females that use flurazepam late in pregnancy can result in sedation (respiratory depression, lethargy, hypotonia) and/or withdrawal symptoms (hyperreflexia, irritability, restlessness, tremors, inconsolable crying, and feeding difficulties) in newborns [see Warnings and Precautions (5.9), Use in Specific Populations (8.1)] . Instruct patients to inform their healthcare provider if they are pregnant.

Advise patients that there is a pregnancy exposure registry that monitors pregnancy outcomes in women exposed to flurazepam during pregnancy [see Use in Specific Populations (8.1)].

Lactation

Advise patients that breastfeeding is not recommended during treatment with flurazepam [see Use in Specific Populations (8.2)] .

Manufactured for:

Chartwell RX, LLC.

Congers, NY 10920

Revised: 12/2023

L71652

Print Medication Guides at: www.chartwellpharma.com/medguides

Print Medication Guides at: www.chartwellpharma.com/medguides

Medication Guide
Flurazepam Hydrochloride Capsules, USP
(flur az' e pam hye" droe klor' ide)

What is the most important information I should know about flurazepam hydrochloride capsules?

- Flurazepam hydrochloride capsules are a benzodiazepine medicine. Taking benzodiazepines with opioid medicines, alcohol, or other central nervous system(CNS) depressants (including street drugs) can cause severe drowsiness, breathing problems (respiratory depression), coma and death.Get emergency help right away if any of the following happens:
  - shallow or slowed breathing
  - breathing stops (which may lead to the heart stopping)
  - excessive sleepiness (sedation).

Do not drive or operate heavy machinery until you know how taking flurazepam hydrochloride capsules with opioids affect you.

- Riskofabuse, misuse, andaddiction.There is a risk of abuse, misuse, and addiction with benzodiazepines, including flurazepam hydrochloride capsules, which can lead to overdose and serious side effects including coma and death.
  - Serious side effects including coma and death have happened in people who have abused or misused benzodiazepines, including flurazepam hydrochloride capsules.These serious side effects may also include delirium, paranoia, suicidal thoughts or actions, seizures, and difficulty breathing. Call your healthcare provider or go to the nearest hospital emergency room right away if you get any of these serious side effects.
  - You can develop an addiction even if you take flurazepam hydrochloride capsules exactly as prescribed by your healthcare provider.
  - Take flurazepam hydrochloride capsules exactly as your healthcare provider prescribed.
  - Do not share your flurazepam hydrochloride capsules with other people.
  - Keep flurazepam hydrochloride capsules in a safe place and away from children.
- Physical dependence and withdrawal reactions.Flurazepam hydrochloride capsules can cause physical dependence and withdrawal reactions, especially if you continue to take flurazepam hydrochloride capsules for several days to several weeks.
  - Do not suddenly stop taking flurazepam hydrochloride capsules. Stopping flurazepam hydrochloride capsules suddenly can cause serious and life-threatening side effects, including unusual movements, responses, or expressions, seizures, sudden and severe mental or nervous system changes, depression, seeing or hearing things that others do not see or hear, an extreme increase in activity or talking, losing touch with reality, and suicidal thoughts or actions. Call your healthcare provider or go to the nearest hospital emergency room right away if you get any of these symptoms.
  - Some people who suddenly stop benzodiazepines have symptoms that can last for several weeks to more than 12 months, including anxiety, trouble remembering, learning, or concentrating, depression, problems sleeping, feeling like insects are crawling under your skin, weakness, shaking, muscle twitching, burning or prickling feeling in your hands, arms, legs or feet, and ringing in your ears.
  - Physical dependence is not the same as drug addiction. Your healthcare provider can tell you more about the differences between physical dependence and drug addiction.
  - Do not take more flurazepam hydrochloride capsules than prescribed or take flurazepam hydrochloride capsules for longer than prescribed.
- After taking flurazepam hydrochloride capsules, you may get up out of bed while not being fully awake and do an activity that you do not know you are doing. The next morning, you may not remember that you did anything during the night. You have a higher chance for doing these activities if you drink alcohol or take other medicines that make you sleepy with flurazepam hydrochloride capsules. Reported activities include:
  - driving a car (“sleep-driving”) ◦ having sex
  - making and eating food ◦ sleep-walking
  - talking on the phone

Call your healthcare provider right away if you find out that you have done any of the above activities after taking flurazepam hydrochloride capsules.

What are flurazepam hydrochloride capsules?

- Flurazepam hydrochloride capsules are a prescription medicine used to treat certain types of insomnia including difficulty falling asleep, waking up often during the night, or waking up early in the morning.
- Flurazepam hydrochloride is a federal controlled substance (C-IV) because it contains flurazepam that can be abused or lead to dependence.Keep in a safe place to prevent misuse and abuse. Selling or giving away flurazepam hydrochloride capsules may harm others, and is against the law. Tell your healthcare provider if you have ever abused or been dependent on alcohol, prescription medicines or street drugs.
- It is not known if flurazepam hydrochloride capsules are safe and effective in children.

Do not take flurazepam hydrochloride capsules if you:

- are allergic to flurazepam hydrochloride, other benzodiazepines, or any of the ingredients in flurazepam hydrochloride capsules. See the end of this Medication Guide for a complete list of ingredients in flurazepam hydrochloride capsules. Symptoms of a serious allergic reaction can include:
  - swelling of your face, lips, and throat that may cause difficulty breathing or swallowing
  - nausea and vomiting

Before you take flurazepam hydrochloride capsules, tell your healthcare provider about all of your medical conditions, including if you:

- have a history of depression, mental illness or, suicidal thoughts
- have a history of drug or alcohol abuse or addiction
- are pregnant or planning to become pregnant.
  - Taking Flurazepam hydrochloride late in pregnancy may cause your baby to have symptoms of sedation (breathing problems, sluggishness, low muscle tone), and/or withdrawal symptoms (jitteriness, irritability, restlessness, shaking, excessive crying, feeding problems).
  - Tell your healthcare provider right away if you become pregnant or think you are pregnant during treatment with Flurazepam hydrochloride.
  - There is a pregnancy registry for women who take Flurazepam hydrochloride during pregnancy. The purpose of the registry is to collect information about the health of you and your baby. If you become pregnant during treatment with Flurazepam hydrochloride, talk to your healthcare provider about registering with the National Pregnancy Registry for Psychiatric Medications. You can register by calling 1-866-961-2388 or visiting https://womensmentalhealth.org/pregnancyregistry/.
- are breastfeeding, or plan to breastfeed.
  - Talk to your healthcare provider about the best way to feed your baby if you take flurazepam hydrochloride capsules.
  - Breastfeeding is not recommended during treatment with Flurazepam hydrochloride.

Tell your healthcare provider about all of the medicines you take,including prescription and over-the-counter medicines, vitamins, and herbal supplements.

Taking flurazepam hydrochloride capsules with certain other medicines can cause side effects or affect how well flurazepam hydrochloride capsules or the other medicines work. Do not start or stop other medicines without talking to your healthcare provider.

Do not take flurazepam hydrochloride capsules with other medicines that can make you sleepy unless your healthcare provider tells you to.

How should I take flurazepam hydrochloride capsules?

- See “What is the most important information I should know about flurazepam hydrochloride capsules?”
- Take flurazepam hydrochloride capsules exactly as your healthcare provider tells you to take it.
- Take flurazepam hydrochloride capsules right before you get into bed.
- Do not take flurazepam hydrochloride capsules unless you are able to get a full night’s sleep before you must be active again.
- If you take too many flurazepam hydrochloride capsules, get emergency treatment right away.

What are the possible side effects of flurazepam hydrochloride capsules? Flurazepam hydrochloride capsules may cause serious side effects, including:

- See “What is the most important information I should know about flurazepam hydrochloride capsules?”
- Other conditions.Call your healthcare provider if your insomnia worsens or is not better within 7 to 10 days. This may mean that there is another condition causing your sleep problem.
- Severe allergic reactions.Symptoms include swelling of the tongue or throat, and trouble breathing. Other symptoms may include nausea and vomiting. Get emergency medical help right away if you have these symptoms after taking flurazepam hydrochloride capsules.
- Abnormal thoughts and behavior.Symptoms include more outgoing or aggressive behavior than normal, confusion, agitation, hallucinations, worsening of depression, and suicidal thoughts.
- Flurazepam hydrochloride capsules can make you sleepy or dizzy and can slow your thinking and motor skills.
  - Do not drive, operate heavy machinery, or do other dangerous activities until you know how flurazepam hydrochloride capsules affect you.
  - Do not drink alcohol or take other drugs that may make you sleepy or dizzy while taking flurazepam hydrochloride capsules without first talking to your healthcare provider. When taken with alcohol or drugs that cause sleepiness or dizziness, flurazepam hydrochloride capsules may make your sleepiness or dizziness much worse.
- Depression.Pre-existing depression may emerge or worsen during use of benzodiazepines including flurazepam hydrochloride capsules.

The most common side effects of flurazepam hydrochloride capsules include:

• dizziness • drowsiness

• light-headedness • staggering

• loss of coordination • falling

These are not all the possible side effects of flurazepam hydrochloride capsules. Call your doctor for medical advice about side effects. You may report side effects to FDA at 1-800- FDA-1088.

How should I store flurazepam hydrochloride capsules?

- Store at 20° to 25°C (68° to 77°F).
- Keep flurazepam hydrochloride capsules in a tightly closed container and out of the light.
- Keep flurazepam hydrochloride capsules and all medicines out of the reach of children.

General information about the safe and effective use of flurazepam hydrochloride capsules.

Medicines are sometimes prescribed for purposes other than those listed in a Medication Guide. Do not use flurazepam hydrochloride capsules for a condition for which it was not prescribed. Do not give flurazepam hydrochloride capsules to other people, even if they have the same symptoms that you have. It may harm them. You can ask your healthcare provider or pharmacist for information about flurazepam hydrochloride capsules that is written for healthcare professionals.

What are the ingredients in flurazepam hydrochloride capsules?

Active Ingredient:flurazepam hydrochloride

Inactive Ingredients:Anhydrous lactose, colloidal silicon dioxide, gelatin, FD&C Blue #1, FD&C Red #3, mannitol, magnesium stearate, talc, and titanium dioxide.

Additionally, capsule shells of 15 mg and 30 mg are imprinted with black pharmaceutical ink. The compositions of the black pharmaceutical ink are black iron oxide, butyl alcohol, dehydrated alcohol, isopropyl alcohol, potassium hydroxide, propylene glycol, purified water, shellac, and strong ammonia solution.

Manufactured for:
Chartwell RX, LLC.
Congers, NY 10920

Revised: 09/2023

L71653

If you would like more information, call Chartwell RX, LLC. at 1-845-232-1683.

This Medication Guide has been approved by the U.S. Food and Drug Administration.

PACKAGE LABEL.PRINCIPAL DISPLAY PANEL

Flurazepam Hydrochloride Capsules, USP CIV - 15 mg - NDC-62135-736-30 - Bottle Label

Flurazepam Hydrochloride Capsules, USP CIV - 15 mg - NDC-62135-736-90 - Bottle Label

Flurazepam Hydrochloride Capsules, USP CIV - 30 mg - NDC-62135-737-30 - Bottle Label

Flurazepam Hydrochloride Capsules, USP CIV - 30 mg - NDC-62135-737-90 - Bottle Label